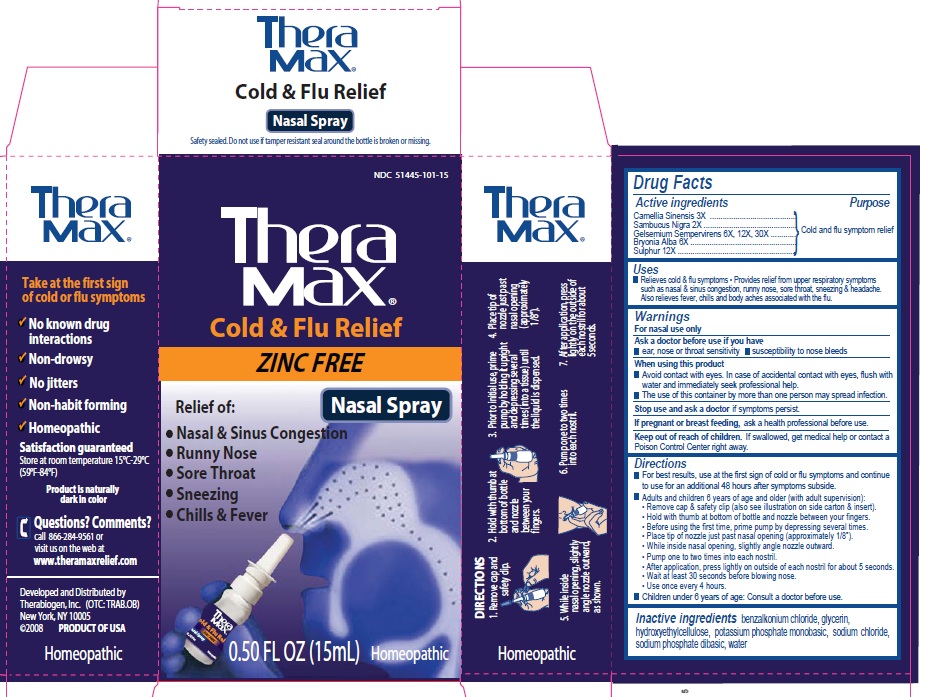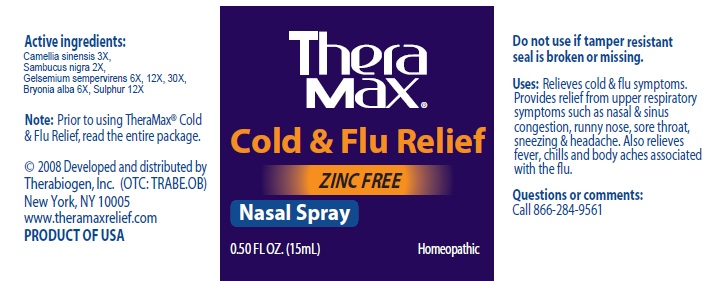 DRUG LABEL: THERABIOGEN COLD AND FLU RELIEF NASAL
NDC: 51445-101 | Form: SPRAY
Manufacturer: THERABIOGEN
Category: homeopathic | Type: HUMAN OTC DRUG LABEL
Date: 20101006

ACTIVE INGREDIENTS: GREEN TEA LEAF 3 [hp_X]/15 mL; SAMBUCUS NIGRA FLOWERING TOP 2 [hp_X]/15 mL; GELSEMIUM SEMPERVIRENS ROOT 6 [hp_X]/15 mL; BRYONIA ALBA ROOT 6 [hp_X]/15 mL; SULFUR 12 [hp_X]/15 mL
INACTIVE INGREDIENTS: BENZALKONIUM CHLORIDE; GLYCERIN; POTASSIUM PHOSPHATE, MONOBASIC; SODIUM CHLORIDE; SODIUM PHOSPHATE, DIBASIC; WATER

THERAMAX COLD & FLU RELIEF NASAL SPRAY

Drug Facts

Active Ingredients Purpose

Camellia Sinensis 3X Cold and Flu Symptom Relief

Sabmucus Nigra 2X Cold and Flu Symptom Relief

Gelsemium sempervirens 6X, 12X 30X Cold and Flu Symptom Relief

Bryonia alba 6X Cold and Flu Symptom Relief

Sulphur 12X Cold and Flu Symptom Relief

Purpose

Cold and flu symptom relief

Uses

Relieves old and flu symptoms

Provides relief from upper respiratory symptoms such as nasal and sinus congestion, runny nose, sore throat, sneezing and headache

Also relieves fever, chills and body aches associated with the flu

Warnings

For nasal use only

Ask a doctor before use if you have

ear, nose or throat sensitivity

susceptible to nose bleeds

When using this product

Avoid contact with eyes. In case of accidental contact with eyes, flush with water and immediately seek professional help.

The use of this container by more than one person may spread infection.

Stop use and ask a doctor if symptoms persist

PREGNANCY OR BREAST FEEDING

If pregnant of breast feeding, ask a health professional before use.

Keep out of reach of children. If swallowed, get medical help or contact a a Poison Control Center right away.

Directions

For best results, use at the first sign of cold or flu symptoms and continue to use for an additional 48 hours after symptoms subside

Adults and children 6 years of age and older (with adult supervision):

Remove cap and safety clip also see illustration on side carton and insert).

Hold with thumb at bottom of bottle and nozzle between your fingers

Before using the first tie, prime pump by depressing several times.

Place tip of nozzle just past nazal opening (approxiately 1/8").

While inside nasal opening, slightly angle nozzle outward.

Pump one to tw times into each nostril

After application, press lightly on outside of each nostril for about 5 seconds.

Wait at least 30 seconds before blowing nose

Use once every 4 hours

Children under 6 years of age: consult a doctor before use.

Inactive Ingredients

Benzalkonium chloride, glyerin, hydroxyethylcellulose, potassium phosphate monobasic, sodium chloride, sodium phosphate dibasic, water

PACKAGE LABEL

Theramax

Take at the first sign of cold or flu symptoms

No known drug interactions

Non-drowsy

No jitters

Non-habit forming

Homeopathic

Satisfaction guaranteed

Store at room temperature 15C-29C (59F-84F)

Product is naturally dark in color

Questions? Comments?
call 866-284-9561 or visit us on the web at
www.theramaxrelief. com
Developed and distributed by
Therabiogen, Inc. (OTC: TRAB.OB)
New York, NY 10005
(c) 2008 PRODUCT OF USA
HOMEOPATHIC

Theramax

Cold and flu relief

ZINC FREE

Nasal Spray

Relief of:

Nasal and Sinus Congestion

Runny Nose

Sore Throat

Sneezing

Chills and Fever

0.50 fl oz (15 ml) Homeopathic

TheraMax

DIRECTIONS

1. Remove cap and safety clip

2. Hold with thumb at bottom and nozzle between your fingers

3. Prior to initial use, prime pump by holding it upright and depressing several ties (into a tissue) until the liquid is dispensed

4. Place tip of nozzle just past nasal opening (approximately 1/8")

5. While inside nasal opening, slightly angle nozzle outward, as shown

6. Pump one to two times into each nostril

7. After application, press lightly on the outside of each nostril for about 5 seconds.

PACKAGE LABEL

Active Ingredients:

Camellia simensis 3X,

Sambucus nigra 2X

Gelsemium sempervirens 6X, 12X, 30X

Bryonica Alba 6X

Sulphur 12X

Note: Prior to using TheraMax Cold and Flu Relief, read the entire package

(c) 2008 Developed and distributed by Therabiogen, Inc. (OTC: TRABE.OB)

New York, NY 10005

www.theramaxrelief.com

PRODUCT OF USA

TheraMax

Cold and Flu Relief

Zinc Free

Nasal Spary

0.50 fl oz (15 ml) Homeopathic

Do not use if tamper resistant seal is broken or missing.

Uses: Relieves cold and flu symptoms. Provides relief from upper respiratory symptoms such as nasal and sinus congestion, runny nose, sore throat, sneezing and headach. Also relieves fever, chills, ad body aches associated with the flu.

Questions or commeents:

Call 866-284-9561